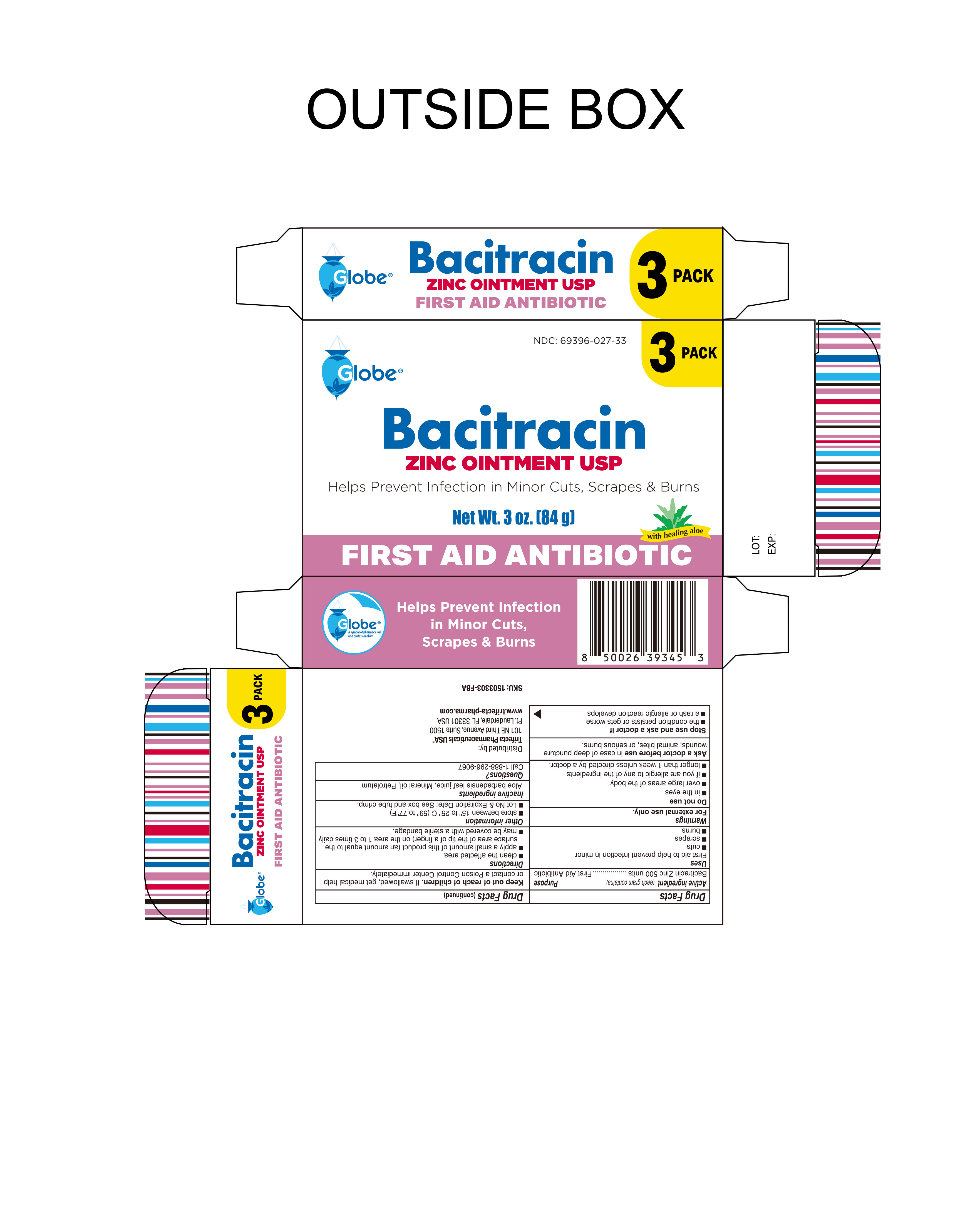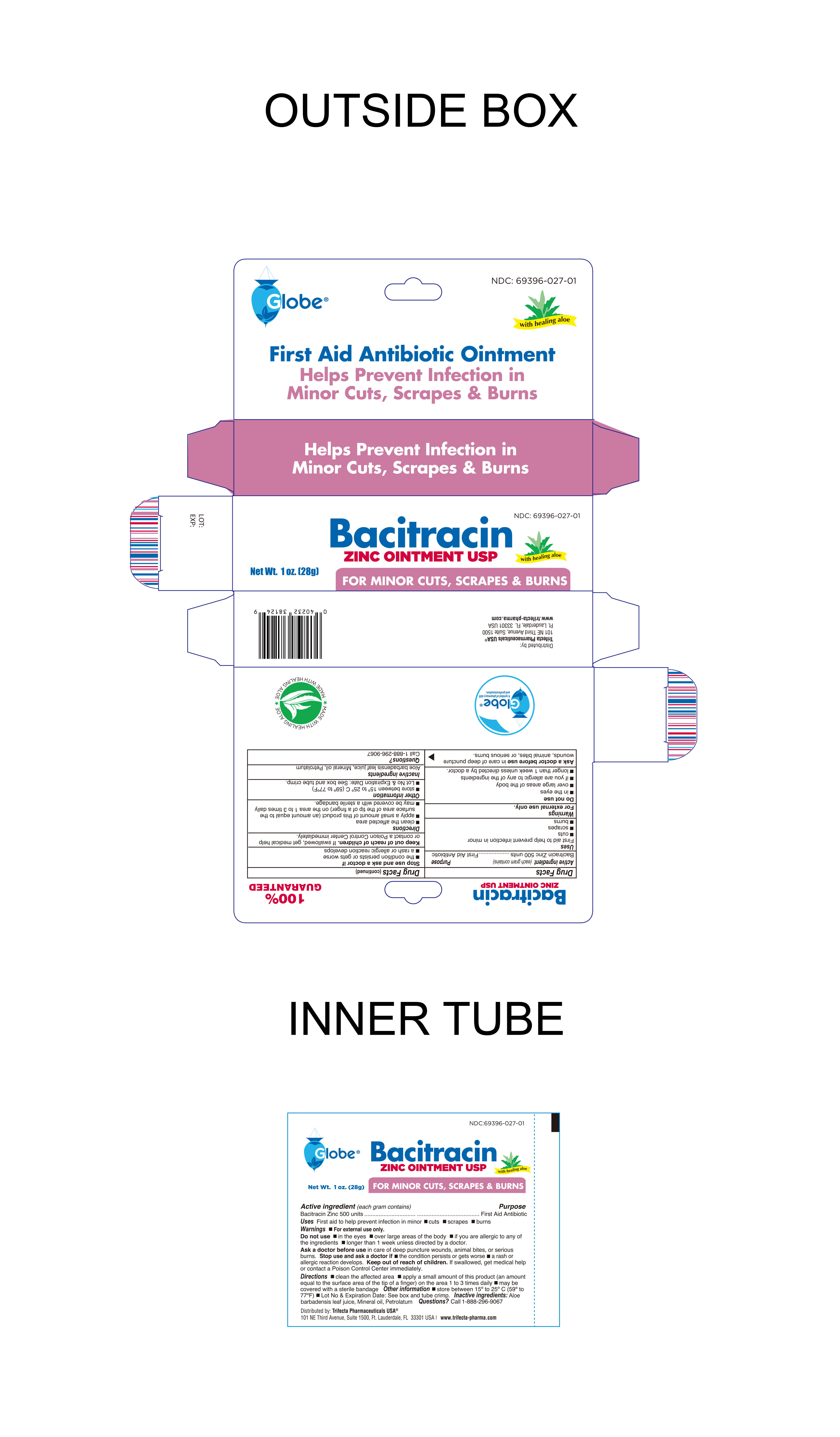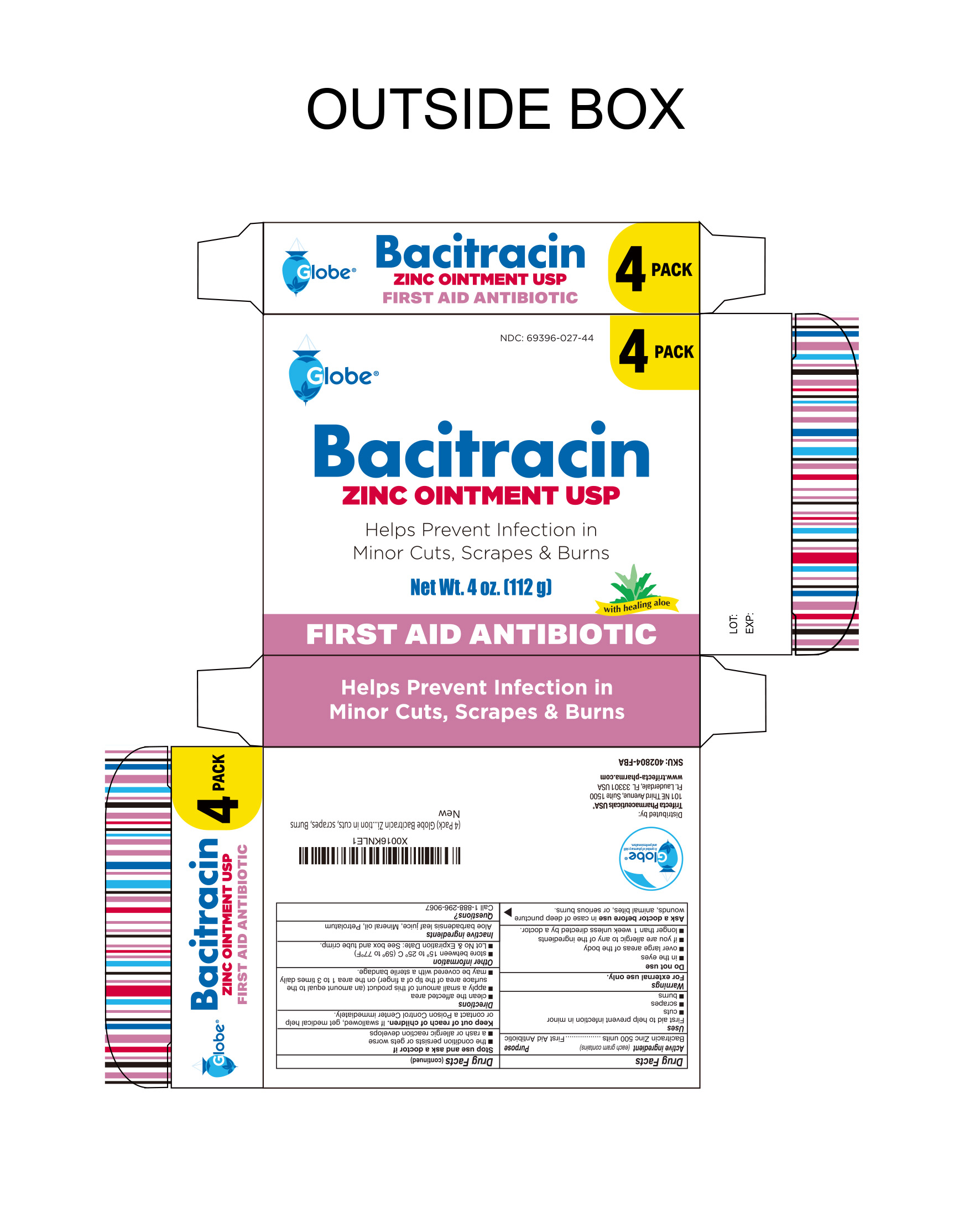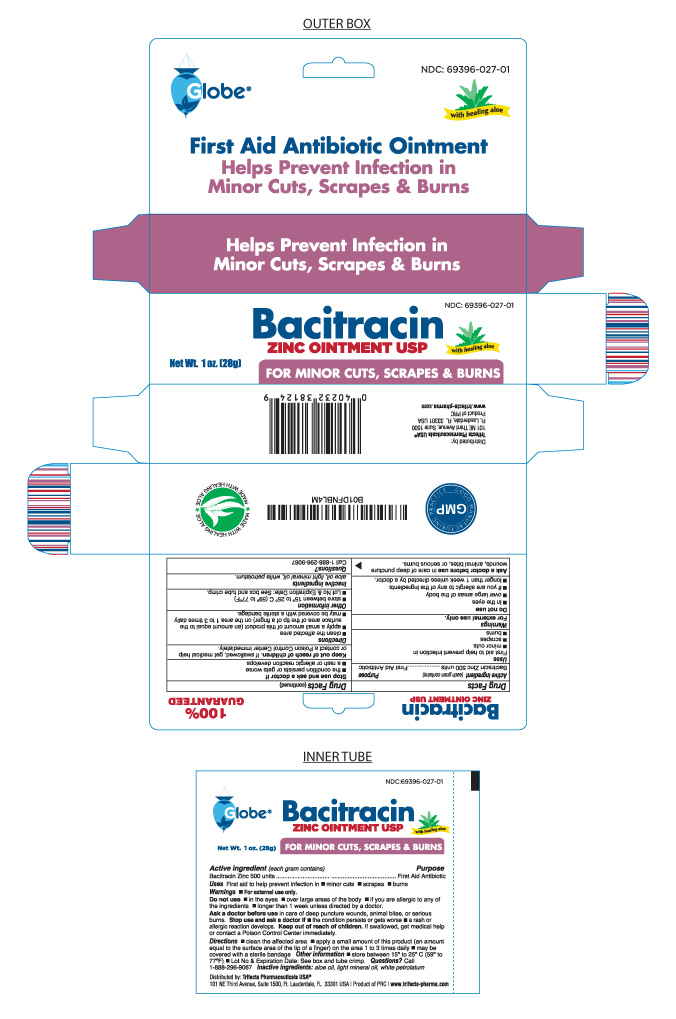 DRUG LABEL: Bacitracin
NDC: 69396-027 | Form: OINTMENT
Manufacturer: Trifecta Pharmaceuticals USA, LLC.
Category: otc | Type: HUMAN OTC DRUG LABEL
Date: 20250515

ACTIVE INGREDIENTS: BACITRACIN ZINC 500 [USP'U]/1 g
INACTIVE INGREDIENTS: MINERAL OIL; PETROLATUM; ALOE VERA LEAF

Bacitracin Zinc Ointment USP

Active Ingredient

Bacitracin Zinc 500 Units per gram

Purpose

First Aid Antibiotic

Uses

First Aid to help prevent infection in

- minor cuts
- scrapes
- burns

Warnings

For External Use Only.

Do not use; in eyes, over large areas of the body, if you are allergic to any of the ingredients, longer than 1 week unless directed by a doctor.

.

Stop Use and Ask Doctor if

- The condition persists or gets worse
- A rash or allergic reaction develops

Directions

- Clean the affected area
- Apply a small amount of this product (an amount equal to the surface area of the tip of a finger) on the area 1 to 3 times daily
- May be covered with a sterile bandage

Inactive Ingredients

Aloe vera gel, light mineral oil, white petrolatum

Other Information

Store between 15º to 25ºC (59º to 77ºF)

Lot No and Expiration Dates - please see box and tube crimp

100% GUARANTEED

Distributed By:

Trifecta Pharmaceuticals USA ®

101 NE Third Avenue, Suite 1500

Ft. Lauderdale, FL. 33301 USA

www.trifecta-pharma.com

Keep out of reach of children

If swallowed, get medical help or contact a Poison Control Center immediately